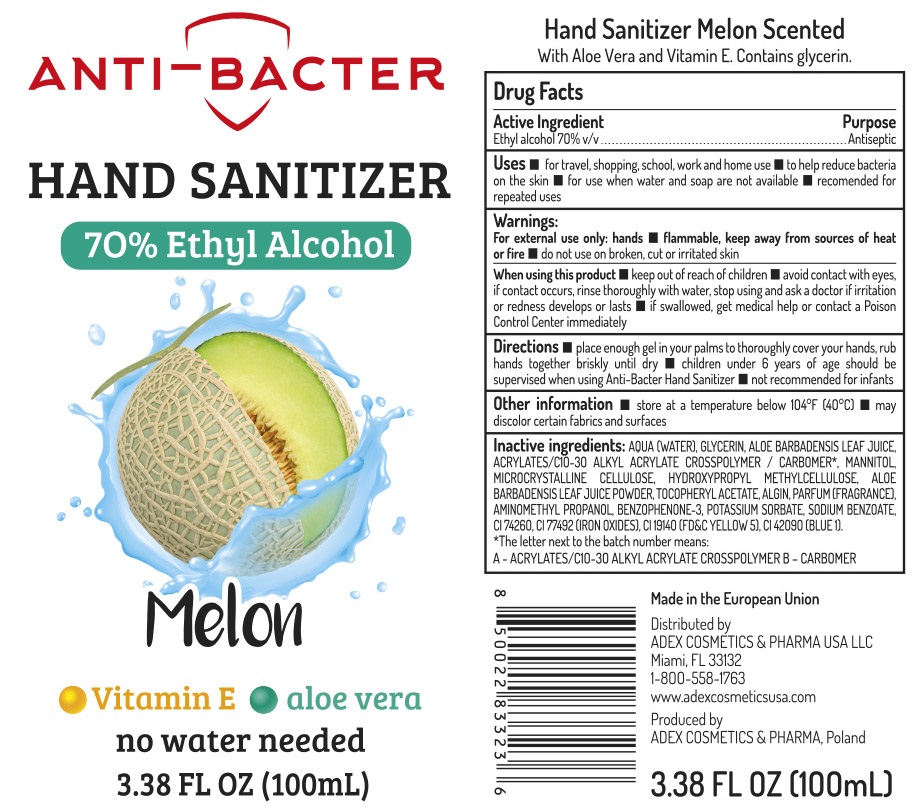 DRUG LABEL: Anti-Bacter Hand Sanitizer 70 Ethyl Alcohol Melon
NDC: 80457-005 | Form: GEL
Manufacturer: ADEX COSMETICS & PHARMA LESZEK SIERDZINSKI
Category: otc | Type: HUMAN OTC DRUG LABEL
Date: 20210308

ACTIVE INGREDIENTS: ALCOHOL 70 mL/100 mL
INACTIVE INGREDIENTS: WATER; GLYCERIN; ALOE VERA LEAF; MANNITOL; MICROCRYSTALLINE CELLULOSE; HYPROMELLOSE, UNSPECIFIED; .ALPHA.-TOCOPHEROL ACETATE; SODIUM ALGINATE; AMINOMETHYLPROPANOL; OXYBENZONE; POTASSIUM SORBATE; SODIUM BENZOATE; FERRIC OXIDE YELLOW; FD&C YELLOW NO. 5; FD&C BLUE NO. 1

Anti-Bacter Hand Sanitizer 70% Ethyl Alcohol Melon

Active Ingredient

Ethyl alcohol 70% v/v

Purpose

Antiseptic

Uses

- for travel, shopping, school, work and home use
- to help reduce bacteria on the skin
- for use when water and soap are not available
- recommended for repeated uses

Warnings:

For external use only: hands

- flammable, keep away from sources of heat or fire

do not use

- on broken, cut or irritated skin

Keep out of reach of children.

- avoid contact with eyes. if contact occurs, rinse thoroughly with water,

stop using and ak a doctor

if irritation or redness develops or lasts

- if swallowed, get medical help or contact a Poison Control Center immediately

Directions

- place enough gel in your palms to thoroughly cover hand, rub hands together brikly until dry
- children under 6 years of age should be supervised when using Anti-Bacter Hand Sanitizer
- not recommended for infants

Other information

- store at a temperature below 104°F (40°C)
- may discolor certain fabrics and surfaces

Inactive Ingredients:

AQUA (WATER), GLYCERIN, ALOE BARBADENSIS LEAF JUICE, ACRYLATES/C10-30 ALKYL ACRYLATE CROSSPOLYMER / CARBOMER*, MANNITOL, MICROCRYSTALLINE CELLULOSE, HYDROXYPROPYL METHYLCELLULOSE, ALOE BARBADENSIS LEAF JUICE POWDER, TOCOPHERYL ACETATE, ALGIN, PARFUM (FRAGRANCE), AMINOMETHYL PROPANOL, BENZOPHENONE-3, POTASSIUM SORBATE, SODIUM BENZOATE, CI 74260, CI 77492 (IRON OXIDES), CI 19140 (FD&C YELLOW 5), CI 42090 (BLUE 1).
*The letter next to the batch number means:
A-ACRYLATES/C10-30 ALKYL ACRYLATE CROSSPOLYMER B-CARBOMER